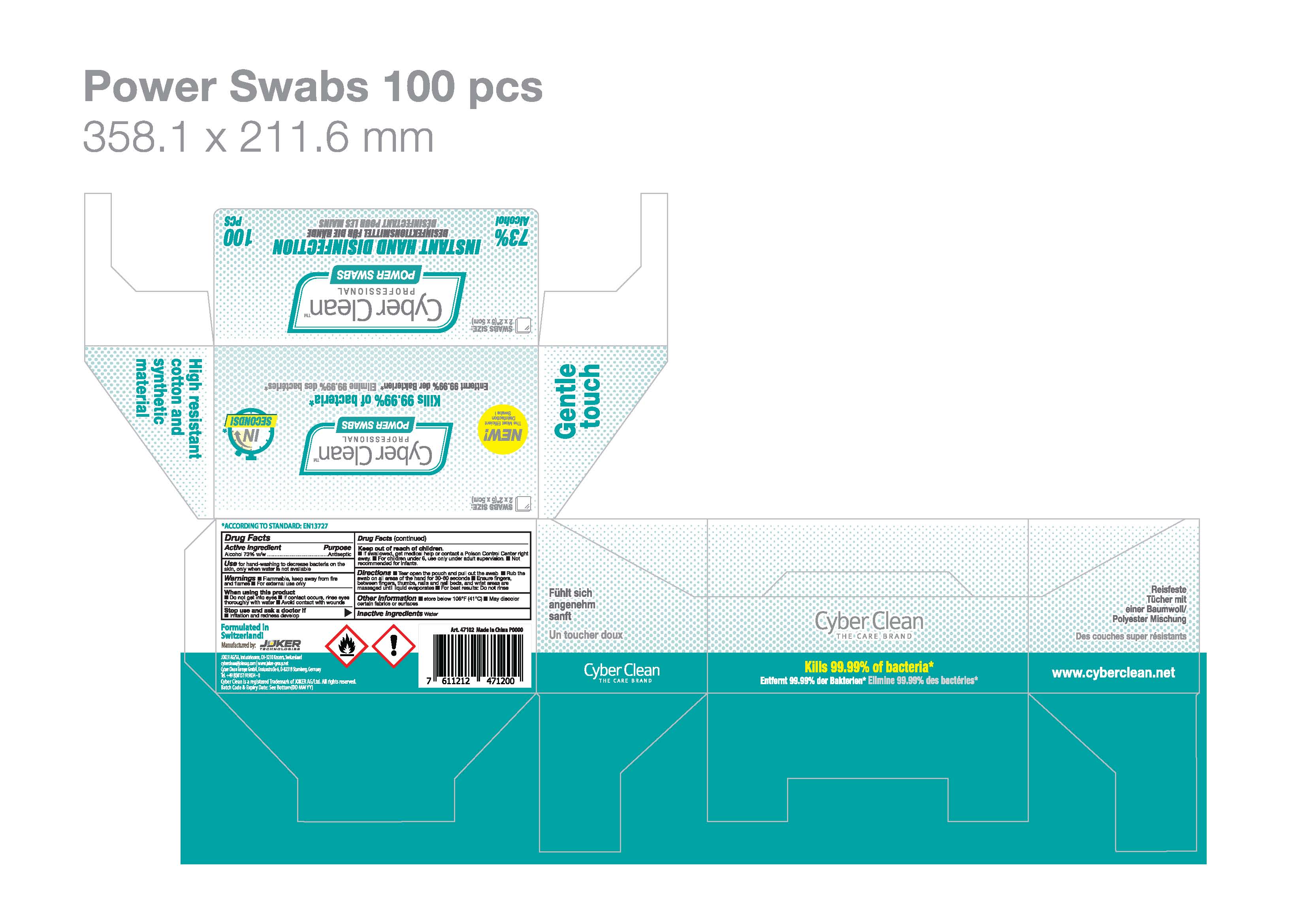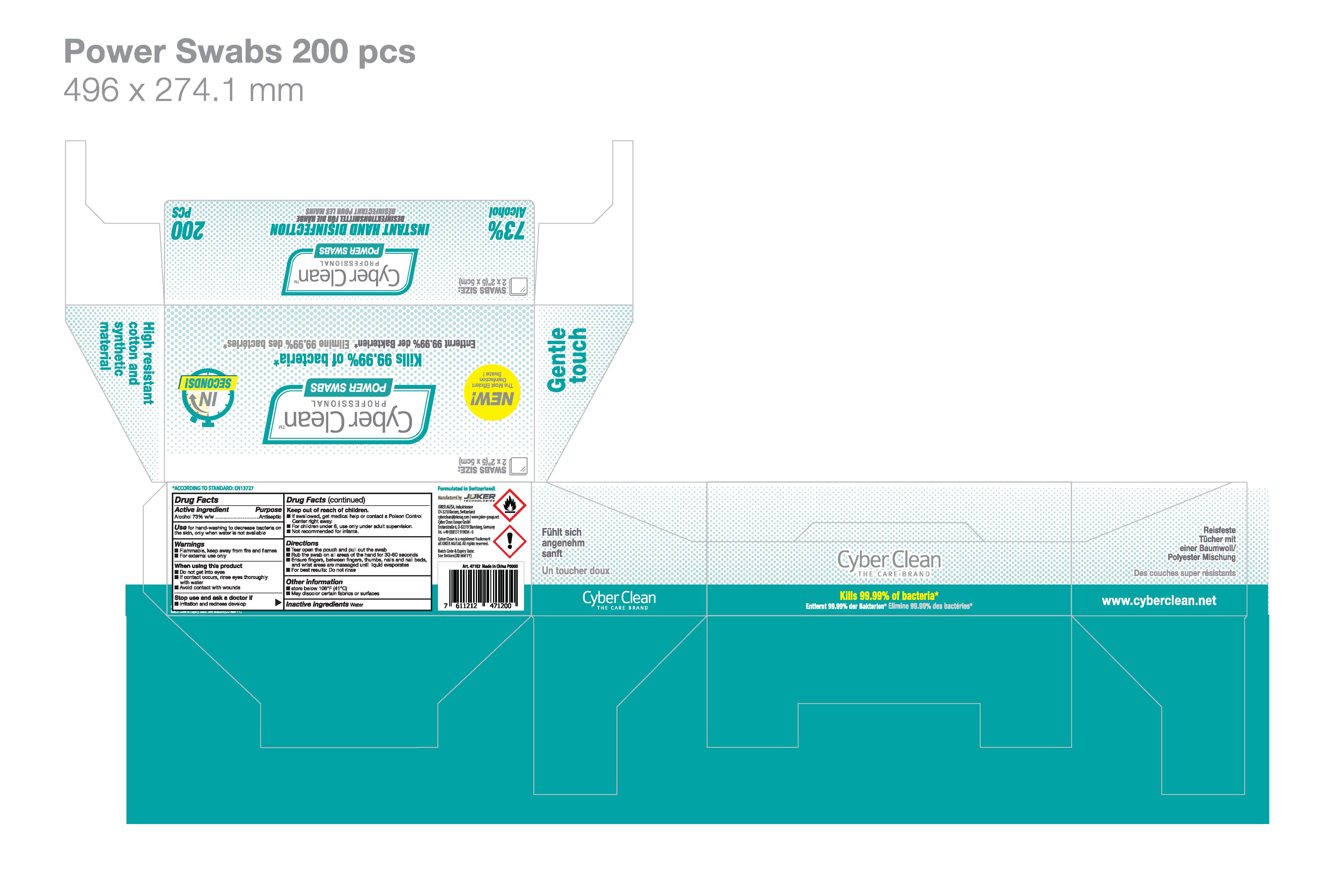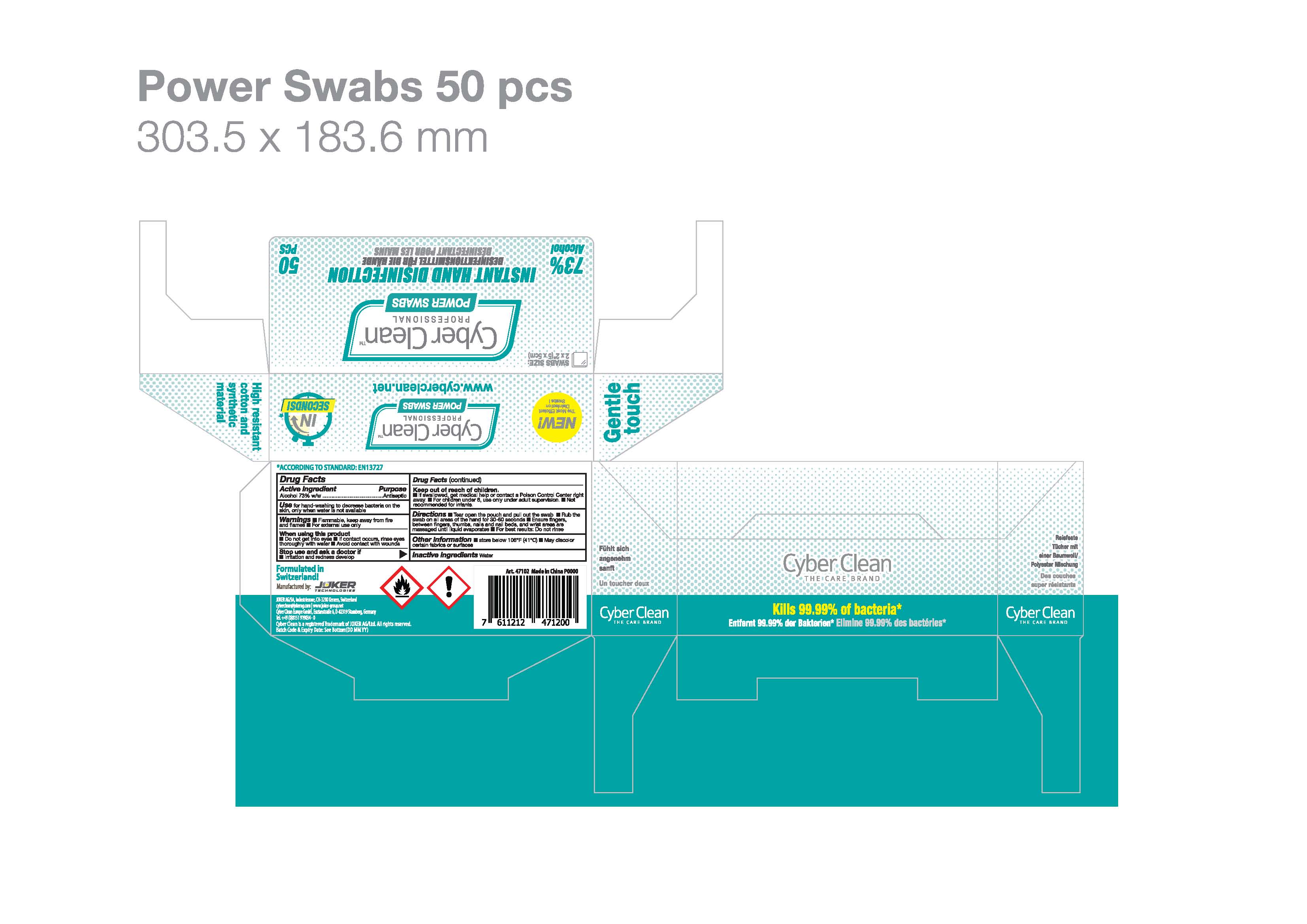 DRUG LABEL: Cyber Clean Professional Power Swabs
NDC: 75757-601 | Form: CLOTH
Manufacturer: JOKER AG
Category: otc | Type: HUMAN OTC DRUG LABEL
Date: 20210126

ACTIVE INGREDIENTS: ALCOHOL 4 mL/1 1
INACTIVE INGREDIENTS: WATER

Cyber Clean Professional Power Swabs

Cyber Clean Professional Power Swabs

Active Ingredient(s)

Alcohol 4mL/pcs. Purpose: Antiseptic

Purpose

Antiseptic, Cyber Clean Professional Power Swabs

Use

Cyber Clean Professional Power Swabs to help reduce bacteria that potentially can cause disease. For use when soap and water are not available.

Warnings

For external use only. Flammable. Keep away from heat or flame

Do not use

- in children less than 2 months of age
- on open skin wounds

When using this product keep out of eyes, ears, and mouth. In case of contact with eyes, rinse eyes thoroughly with water.
Stop use and ask a doctor if irritation or rash occurs. These may be signs of a serious condition.
Keep out of reach of children. If swallowed, get medical help or contact a Poison Control Center right away.

Stop use and ask a doctor if irritation or rash occurs. These may be signs of a serious condition.

Keep out of reach of children. If swallowed, get medical help or contact a Poison Control Center right away.

Directions

Open the lid and pull out the wipe.
Keep the lid closed after use to retain moisture.
Rub the wipe on all areas of the hand for 30-60 seconds.
Ensure fingers, between fingers, thumbs, nails and nail beds, and wrist areas are massaged until luquid evaporates.
For best results: Do not rinse.
Supervise children under 6 years of age when using this product to avoid swallowing.

Other information

- Store between 15-30C (59-86F)
- Avoid freezing and excessive heat above 40C (104F)

Inactive ingredients

purified water USP